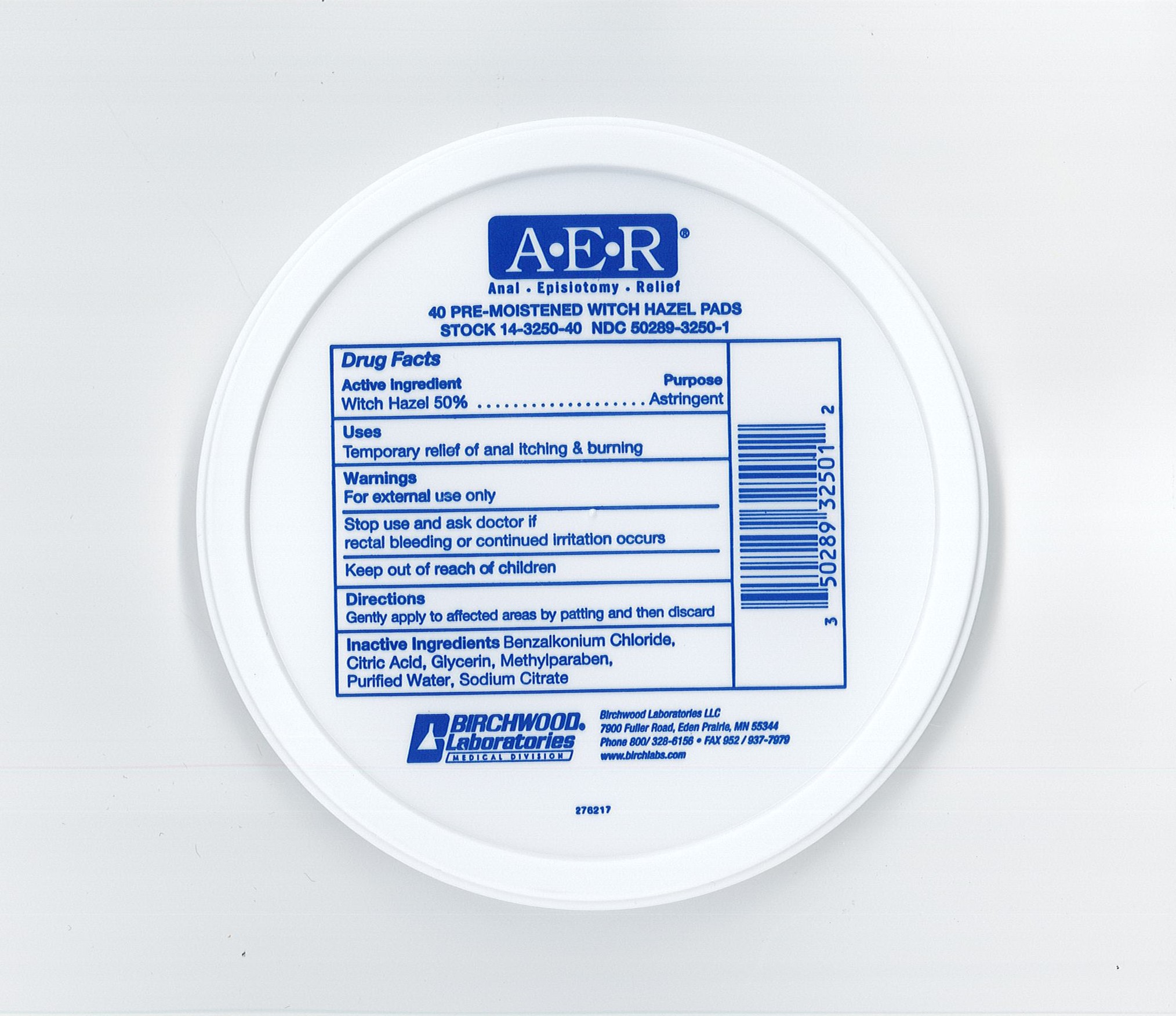 DRUG LABEL: AER
NDC: 50289-3250 | Form: SOLUTION
Manufacturer: Birchwood Laboratories LLC
Category: otc | Type: HUMAN OTC DRUG LABEL
Date: 20250114

ACTIVE INGREDIENTS: WITCH HAZEL 500 mg/1 mL
INACTIVE INGREDIENTS: GLYCERIN; WATER; METHYLPARABEN; BENZALKONIUM CHLORIDE; ANHYDROUS CITRIC ACID; SODIUM CITRATE

AER 40's Drug Facts

Active Ingredient

Witch Hazel 50%

Purpose

Astringent

Uses

Temporary relief of anal itching and burning

Temporarily protects irritated tissues

Warnings

For external rectal use only

Stop use and ask doctor if

rectal bleeding or continued irritation occurs

Keep Out Of Reach of Children

Directions

Gently apply to affected areas by patting and then discard

Inactive Ingredients

Benzalkonium Chloride, Citric Acid, Glycerin, Methylparaben, Purified Water, Sodium Citrate